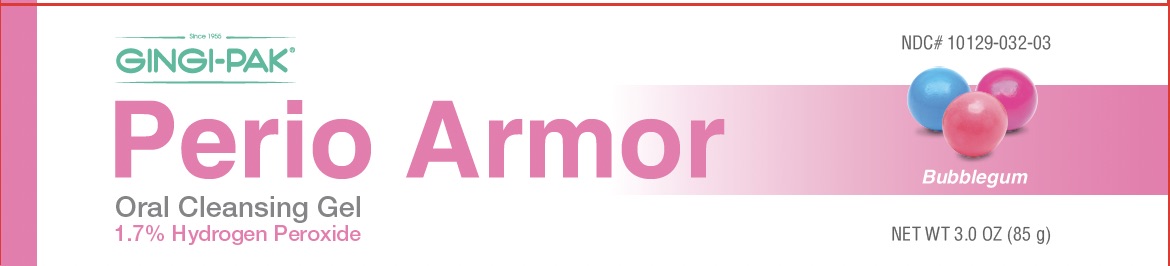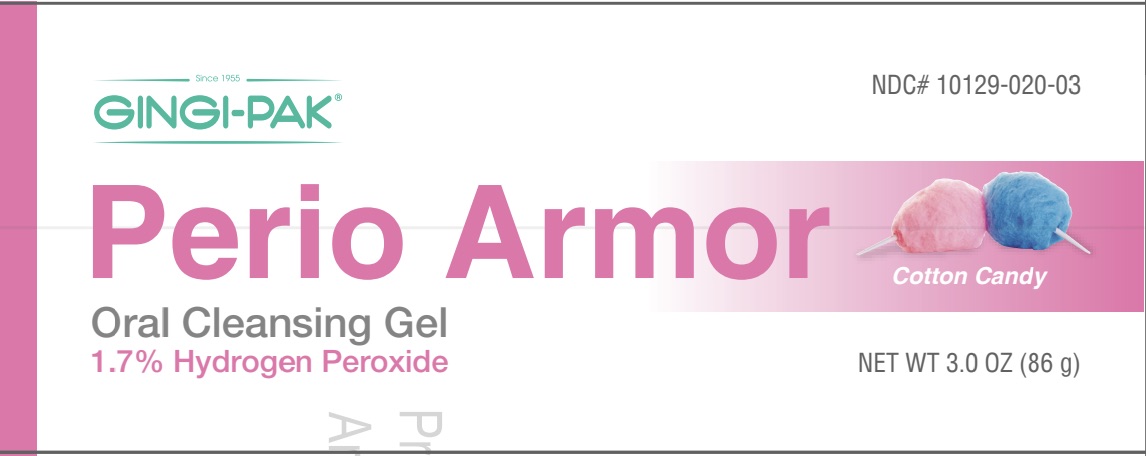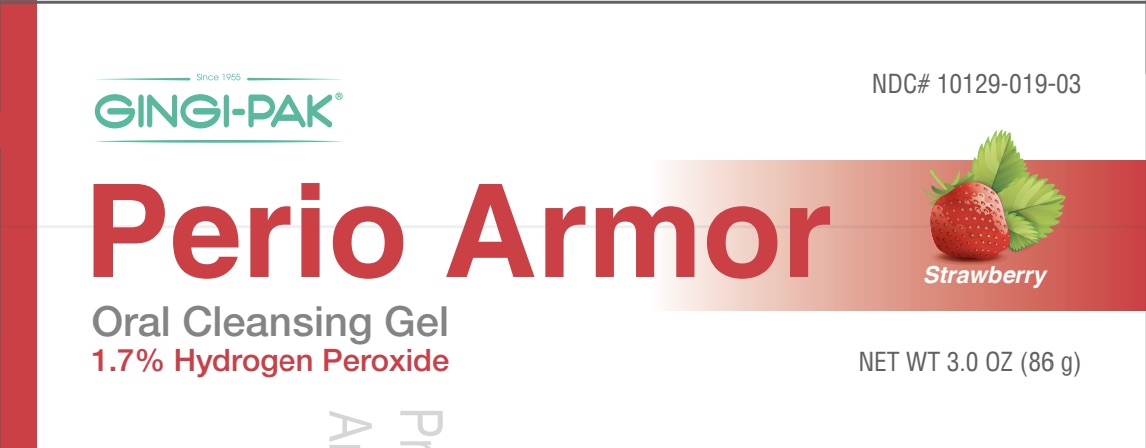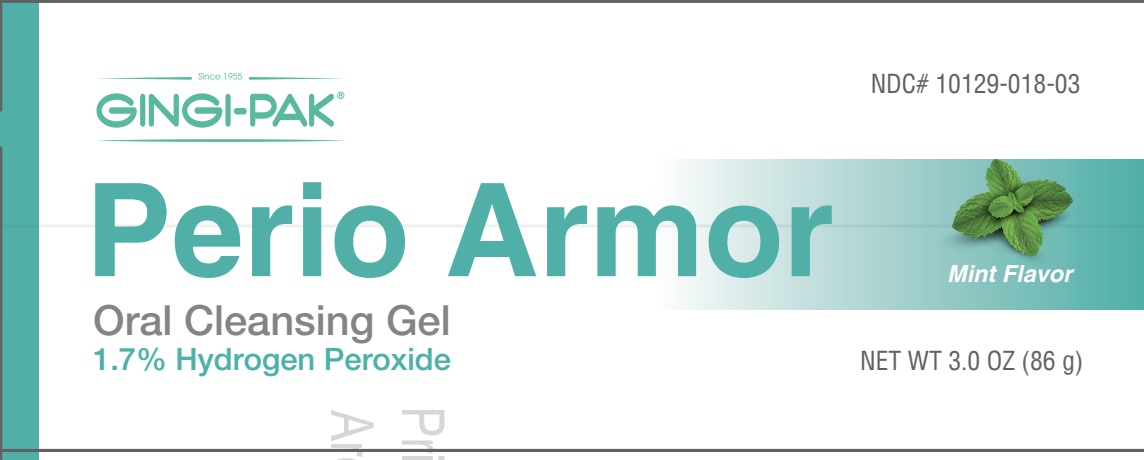 DRUG LABEL: Perio Armor
NDC: 10129-019 | Form: GEL
Manufacturer: Gingi-Pak a Division of the Belport
Category: otc | Type: HUMAN OTC DRUG LABEL
Date: 20251118

ACTIVE INGREDIENTS: HYDROGEN PEROXIDE 17 g/100 mL
INACTIVE INGREDIENTS: EDTA; CARBOMER 940; WATER; SACCHARIN SODIUM; GLYCERIN; 2-AMINO-2-METHYL-1-PROPANOL OLEATE; SODIUM BENZOATE

Perio Armor

Active Ingredient

Hydrogen Peroxide 1.7% (w/w)

Purpose

Wound Cleanser

Indication and Uses

For temporary use in cleansing minor oral wounds and treatment of inflammation resulting from dental procedures or other irritations of the mouth and gums. Perio Armor may be used for decreasing the presence of plaque, a known factor in the development of gingivitis and tooth decay.

Directions

For children under 2 years of age, consult a dentist or physician before use. For adults and children 2 years of age or older: 1. Remove cap and cut the tip of the tube at the narrow end. 2. Apply several drops of the gel directly onto the affected area in the mouth. 3. Leave the gel on the affected area for at least 60 seconds, then spit. 4. Use up to 4 times daily after meals, at bedtime, or as directed by a dentist or physician.

Other Information

Store at room temperature between 20-25° C (68-77° F) and away from direct sunlight. Do not use if the tube has been damaged or tampered in any way

Inactive Ingredients (mint flavor)

Ethyl Alcohol, Menthol, Methyl Salicylate, Phosphoric Acid, Poloxamer 407, Polysorbate 20, Potassium Sorbate, Sodium Saccharin, Sorbitol, Water

Question or comments?

(800)437-1514 or www.gingi-pak.com.

Warning

Do not use Perio Armor for more than 7 days unless directed by your dentist or physician.

Stop use

Stop use and consult your dentist or physician if: • Symptoms do not improve within 7 days • Irritation, pain, or redness persists or worsens • Swelling, rash, or fever develops

Keep out of reach of children.

Inactive Ingredients (Strawberry and Bubblegum)

Ethyl Alcohol, Phosphoric Acide, Poloxamer 407, Polysorbate 20, Potassium Sorbate, Sodium Saccharin, Sorbitol, Water, Natural and Artificial Flavors